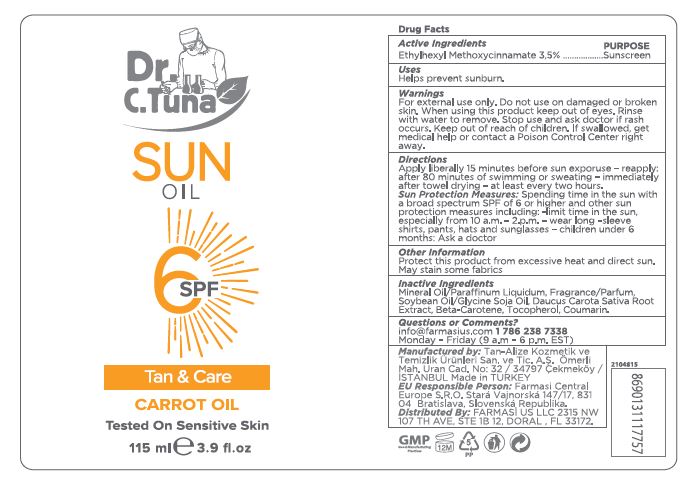 DRUG LABEL: Dr. C. Tuna Sun 6 SPF Tan and Care Carrot
NDC: 74690-002 | Form: OIL
Manufacturer: Farmasi US LLC
Category: otc | Type: HUMAN OTC DRUG LABEL
Date: 20260109

ACTIVE INGREDIENTS: OCTINOXATE 35 mg/1 mL
INACTIVE INGREDIENTS: MINERAL OIL; SOYBEAN OIL; CARROT; BETA CAROTENE; TOCOPHEROL; COUMARIN

Dr. C. Tuna Sun Oil 6 SPF Tan & Care Carrot Oil

Active Ingredients

Ethylhexyl Methoxycinnamate 3,5%

PURPOSE

Sunscreen

Uses

Helps prevent sunburn.

Warnings

For external use only. Do not use on damaged or broken skin. When using this product keep out of eyes. Rinse with water to remove. Stop use and ask doctor if rash occurs.

Keep out of reach of children. If swallowed, get medical help or contact a Poison Control Center right away.

Directions

Apply liberally 15 minutes before sun exposure – reapply: after 80 minutes of swimming or sweating – immediately after towel drying – at least every two hours.

Spending time in the sun with a broad spectrum SPF of 6 or higher and other sun protection measures including: - limit time in the sun, especially from 10 a.m. – 2 p.m. – wear long-sleeve shirts, pants, hats and sunglasses – children under 6 months: Ask a doctor Sun Protection Measures:

Other information

Protect this product from excessive heat and direct sun. May stain some fabrics

Inactive Ingredients

Mineral Oil/Paraffinum Liquidum, Fragrance/Parfum, Soybean Oil/Glycine Soja Oil, Daucus Carota Sativa Root Extract, Beta-Carotene, Tocopherol, Coumarin.

Questions or Comments?

info@farmasius.com 1 786 238 7338

Monday - Friday (9 a.m - 6 p.m. EST)

Manufactured by: Tan-Alize Kozmetik ve Temizlik Ürünleri San. ve. Tic. A.S. Ömerli Mah. Uran Cad. No: 32 / 34797 Cekmeköy / ISTANBUL

Made in TURKEY

EU REsponsible Person: Farmasi Central Europe S.R.O. Stará Vajnorská Republika. Distributed By: FARMASI US LLC 2315 NW 107 TH AVE, STE 1B 12, DORAL , FL 33172.